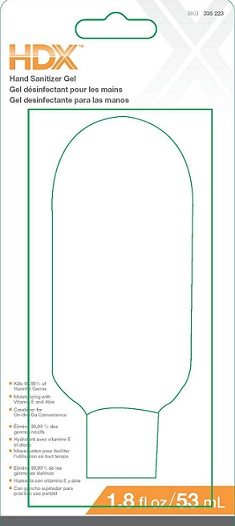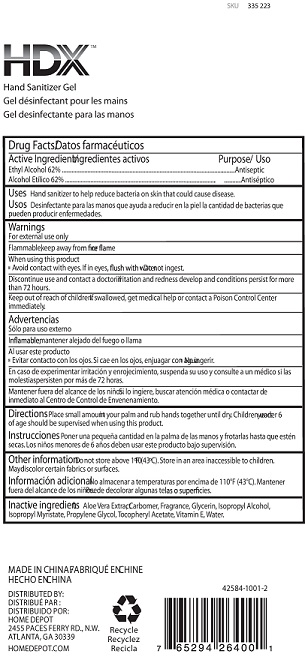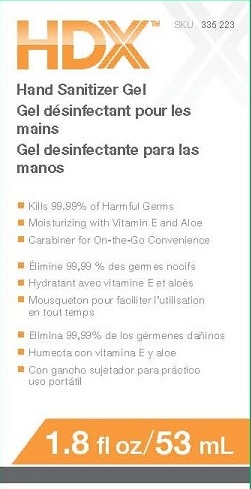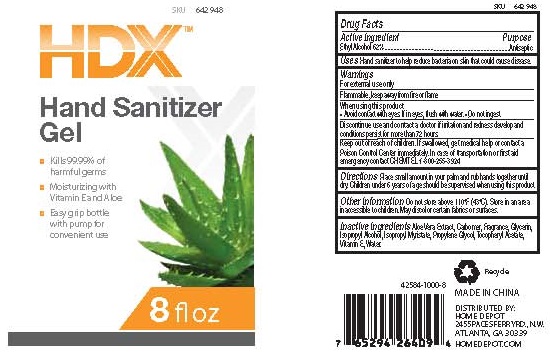 DRUG LABEL: HAND SANITIZER
NDC: 42584-1001 | Form: GEL
Manufacturer: HOME DEPOT U.S.A. INC.
Category: otc | Type: HUMAN OTC DRUG LABEL
Date: 20130408

ACTIVE INGREDIENTS: ALCOHOL 62 mL/100 mL
INACTIVE INGREDIENTS: ALOE VERA LEAF; CARBOMER 940; GLYCERIN; ISOPROPYL ALCOHOL; ISOPROPYL MYRISTATE; PROPYLENE GLYCOL; .ALPHA.-TOCOPHEROL ACETATE, D-; WATER

ACTIVE INGREDIENT
ETHYL ALCOHOL 62% V/V

PURPOSE:

ANTISEPTIC

USES

HAND SANITIZER TO HELP REDUCE BACTERIA ON SKIN THAT COULD CAUSE DISEASE

Warnings
For external use only

Flammable, keep away from fire or flame

Other information Do not store above 110F (43C).
Store in an area inaccessible to children.

When using this product
■ Avoid contact with eyes. If in eyes, flush with water.

■ Do not ingest.

■ Discontinue use and contact a doctor if irritation and redness develop and conditions persist for more than 72 hours.

Keep out of reach of children. If swallowed, get medical help or contact a Poison Control Center immediately. In case of transportaton or first aid emergency contact CHEMTEL 1-800-255-3924.

Directions

Place small amount in your palm and rub hands together until dry. Children under 6 years of age should be supervised when using this product.

Inactive ingredients

Aloe Vera Extract, Carbomer, Fragrance, Glycerin, Isopropyl Alcohol, Isopropyl Myristate, Propylene Glycol, Tocopheryl Acetate,
Vitamin E, Water.